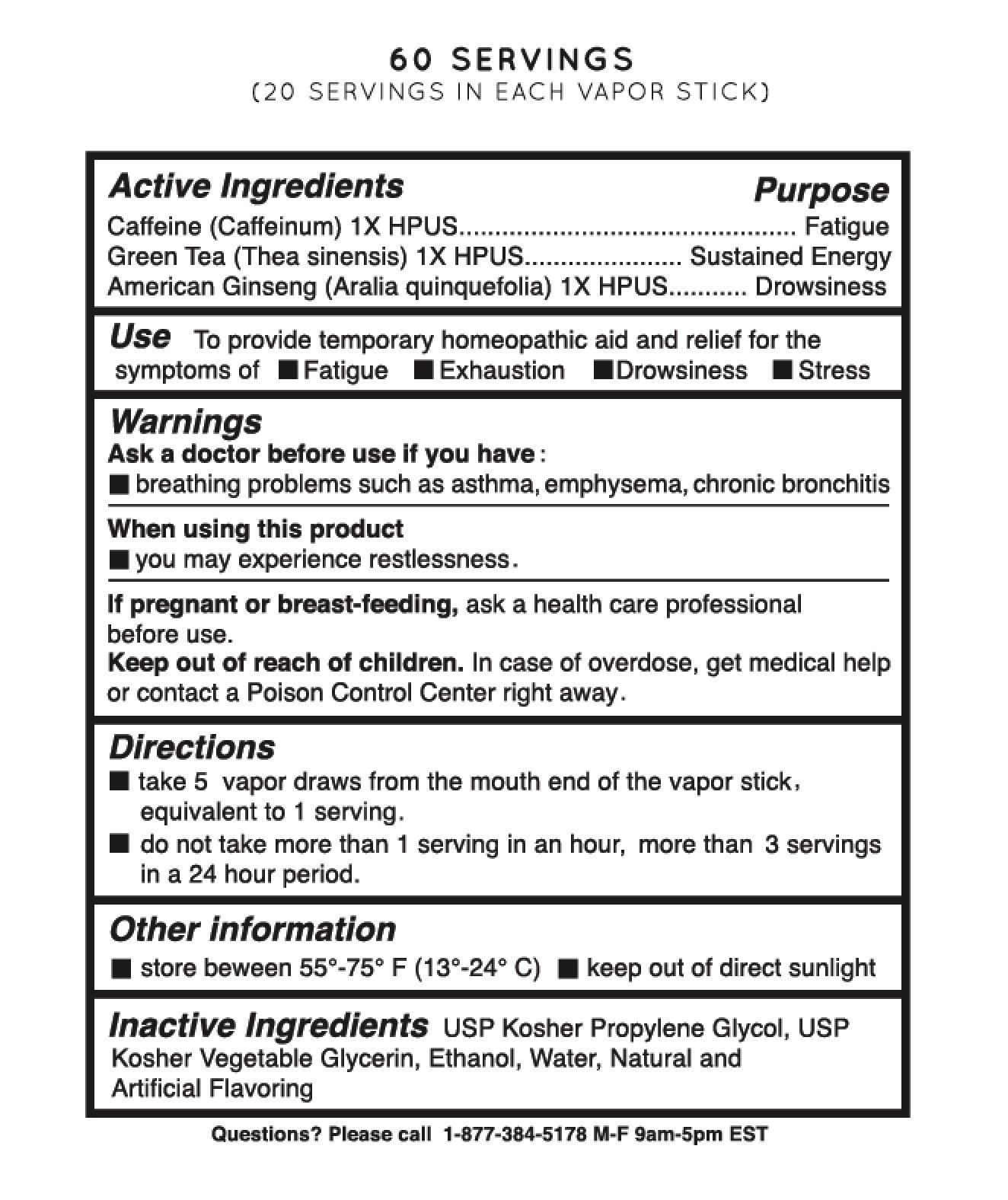 DRUG LABEL: Vapergy
NDC: 69466-001 | Form: SPRAY
Manufacturer: Vapergy USA LLC
Category: homeopathic | Type: HUMAN PRESCRIPTION DRUG LABEL
Date: 20200204

ACTIVE INGREDIENTS: CAFFEINE 1 [hp_X]/0.45 mg; GREEN TEA LEAF 1 [hp_X]/0.45 mg; AMERICAN GINSENG 1 [hp_X]/0.45 mg
INACTIVE INGREDIENTS: PROPYLENE GLYCOL; GLYCERIN; ALCOHOL; WATER

Vapergy

Active Ingredients Purpose

Caffeine (Caffeinum) 1X HPUS ............................................ Fatigue

Green Tea (Thea Sinensis) 1X HPUS ..................... Sustained Energy

American Ginseng (Aralia Quinquefolia) 1X HPUS ........... Drowsiness

Use

to provide temporary homeopathic aid and relief for the symptoms of

- fatigue
- exhaustion
- drowsiness
- stress

Keep out of reach of children. In case of overdose, get medical help or contact a Poison Control Center right away.

INDICATIONS AND USAGE

Vapergy Vapor Stick

Directions

- take 5 vapor draws from the mouth end of the vapor stick, equivalent to 1 serving.
- do not take more than 1 serving in an hour, more than 3 servings in a 24 hour period.

Warnings

Ask a doctor before use if you have:

- breathing problems such as asthma, emphysema, chronic bronchitis

When using this product

- you may experience restlessness.

If pregnant or breast-feeding ask a health care professional before use.

Inactive Ingredients

USP Kosher propylene glycol, USP kosher vegetable glycerin, ethanol, water, natural and artificial flavoring.